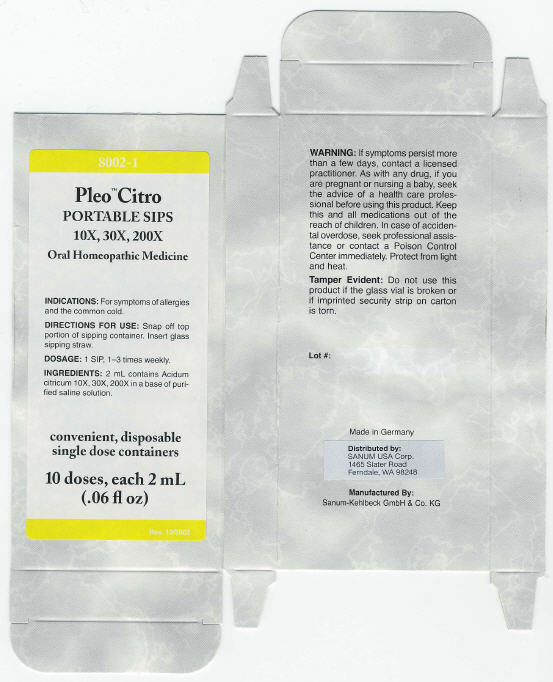 DRUG LABEL: Pleo Citro
NDC: 60681-8002 | Form: LIQUID
Manufacturer: Sanum Kehlbeck GmbH & Co. KG
Category: homeopathic | Type: HUMAN OTC DRUG LABEL
Date: 20091016

ACTIVE INGREDIENTS: citric acid 10 [HP_X]/2 mL; citric acid 30 [HP_X]/2 mL; citric acid 200 [HP_X]/2 mL
INACTIVE INGREDIENTS: water; sodium chloride

Pleo™ Citro
PORTABLE SIPS
10X, 30X, 200X

Oral Homeopathic Medicine

10 doses, each 2 mL
(.06 fl oz)

INDICATIONS

For symptoms of allergies and the common cold.

DIRECTIONS FOR USE

Snap off top portion of sipping container. Insert glass sipping straw.

DOSAGE

1 SIP, 1–3 times weekly.

INGREDIENTS

2 mL contains Acidum citricum 10X, 30X, 200X in a base of purified saline solution.

WARNING

If symptoms persist more than a few days, contact a licensed practitioner. As with any drug, if you are pregnant or nursing a baby, seek the advice of a health care professional before using this product.

KEEP OUT OF REACH OF CHILDREN

Keep this and all medications out of the reach of children. In case of accidental overdose, seek professional assistance or contact a Poison Control Center immediately.

STORAGE AND HANDLING

Protect from light and heat.

Tamper Evident

Do not use this product if the glass vial is broken or if imprinted security strip on carton is torn.

Made in Germany

Distributed by:
SANUM USA Corp.
1465 Slater Road
Ferndale, WA 98248

Manufactured By:
Sanum-Kehlbeck GmbH & Co. KG

Rev. 10/2002

PRINCIPAL DISPLAY PANEL - 2 mL Carton

8002-1

Pleo™ Citro
PORTABLE SIPS
10X, 30X, 200X

Oral Homeopathic Medicine

INDICATIONS: For symptoms of allergies
and the common cold.

DIRECTIONS FOR USE: Snap off top
portion of sipping container. Insert glass
sipping straw.

DOSAGE: 1 SIP, 1–3 times weekly.

INGREDIENTS: 2 mL contains Acidum
citricum 10X, 30X, 200X in a base of puri-
fied saline solution.

convenient, disposable
single dose containers

10 doses, each 2 mL
(.06 fl oz)

Rev. 10/2002